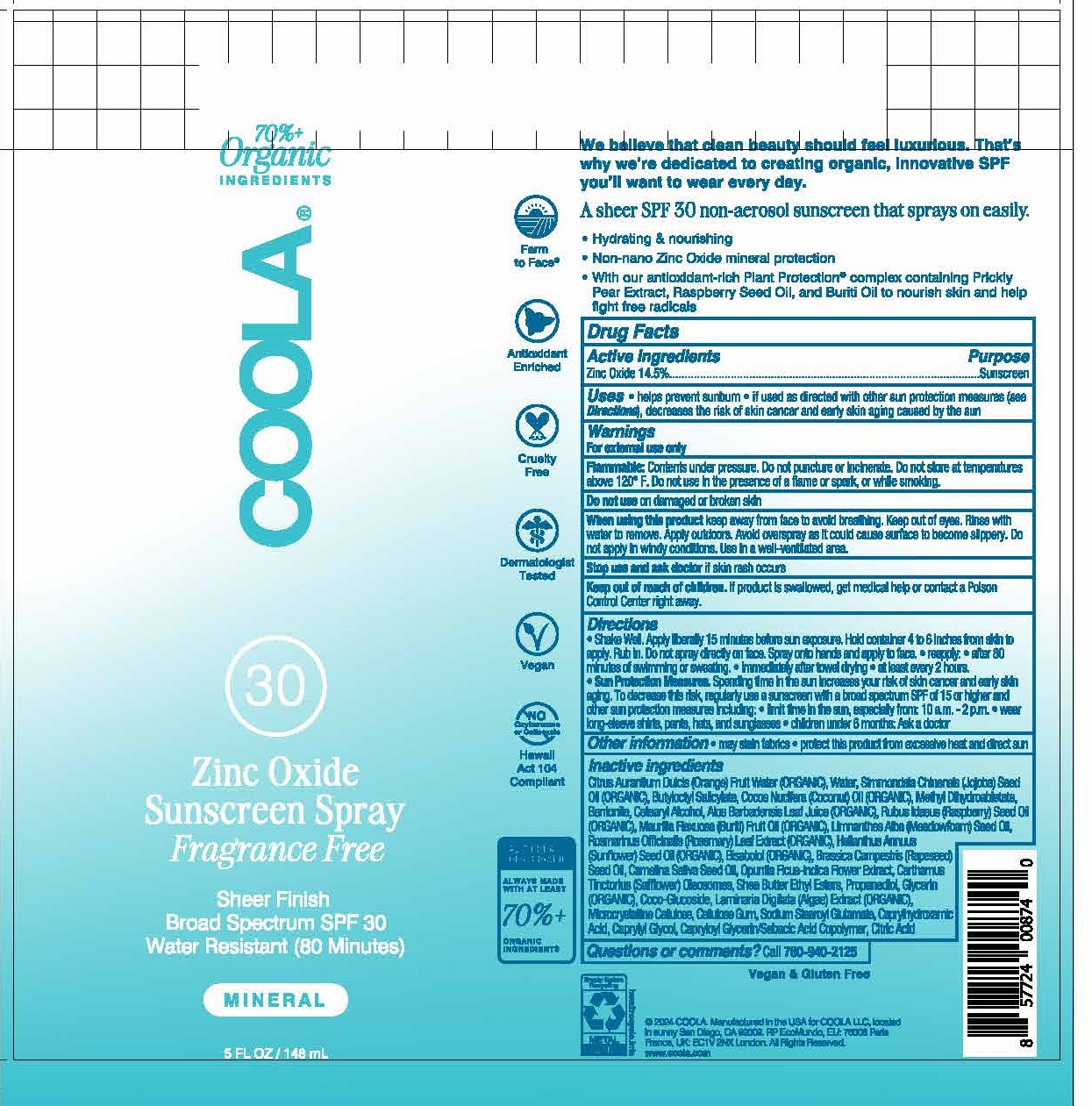 DRUG LABEL: Coola SPF 30 Mineral Sunscreen Fragrance Free
NDC: 79753-049 | Form: SPRAY
Manufacturer: COOLA, LLC
Category: otc | Type: HUMAN OTC DRUG LABEL
Date: 20250214

ACTIVE INGREDIENTS: ZINC OXIDE 14.5 g/100 mL
INACTIVE INGREDIENTS: LAMINARIA DIGITATA; BENTONITE; CAMELINA SATIVA SEED OIL; CAPRYLHYDROXAMIC ACID; CITRIC ACID MONOHYDRATE; SUNFLOWER OIL; LEVOMENOL; BRASSICA RAPA SUBSP. OLEIFERA OIL; CARTHAMUS TINCTORIUS (SAFFLOWER) OLEOSOMES; MICROCRYSTALLINE CELLULOSE; CARBOXYMETHYLCELLULOSE SODIUM, UNSPECIFIED FORM; SODIUM STEAROYL GLUTAMATE; CAPRYLOYL GLYCERIN/SEBACIC ACID COPOLYMER (2000 MPA.S); WATER; CETOSTEARYL ALCOHOL; SHEA BUTTER ETHYL ESTERS; PROPANEDIOL; ALOE VERA LEAF; ROSEMARY; ORANGE; BUTYLOCTYL SALICYLATE; METHYL DIHYDROABIETATE; COCO GLUCOSIDE; GLYCERIN; MEADOWFOAM SEED OIL; CAPRYLYL GLYCOL; JOJOBA OIL; COCONUT OIL; MAURITIA FLEXUOSA FRUIT OIL; RASPBERRY SEED OIL; OPUNTIA FICUS-INDICA FLOWER

Coola Mineral Spray SPF 30 - Unscented

ACTIVE INGREDIENT

Zinc Oxide - 14.5%

PURPOSE

Sunscreen

Uses

• Helps prevent sunburn
• If used as directed with other sun protection measures (see Directions), decreases the risk of skin cancer and early skin aging caused by the sun.

WARNINGS

- For external use only
- Flammable: Contents under pressure. Do not puncture or incinerate. Do not store at temperatures above 120° F. Do not use in the presence of a flame or spark, or while smoking.
- Do not use on damaged or broken skin
- When using this product keep away from face to avoid breathing in • Keep out of eyes. Rinse with water to remove. Apply outdoors. Avoid overspray as could cause surface to become slippery. Do not apply in windy conditions. Use in a well ventilated area.
- Stop use and ask doctor if skin rash occurs

Keep out of reach of children. If product is swallowed, get medical help or contact a Poison Control Center right away.

Directions

• Shake well. Apply liberally 15 minutes before sun exposure. Hold container 4 to 6 inches from skin to apply. Rub in. Do not spray directly on face. Spray onto hands and apply to face. • When properly used, mineral sunscreens will leave a whitish tint when first applied.

• Reapply: • after 80 minutes of swimming or sweating • immediately afrer towel drying • at least every 2 hours
• Sun Protection Measures. Spending time in the sun increases your risk of skin cancer and early skin aging. To decrease this risk, regularly use a sunscreen with a broad spectrum SPF of 15 or higher and other sun protection measures including: • limit time in the sun, especially from: 10 a.m. -2 p.m. • wear long-sleeve shirts, pants, hats, and sunglasses

• Children under 6 months: Ask a doctor

OTHER SAFETY INFORMATION

- May stain fabrics
- Protect this product from excessive heat and direct sun

INACTIVE INGREDIENT

Citrus Aurantium Dulcis (Orange) Fruit Water (ORGANIC), WaterSimmondsia Chinensis (Jojoba) Seed Oil (ORGANIC), Butyloctyl Salicylate, Cocos Nucifera (Coconut) Oil (ORGANIC), Methyl Dihydroabietate, Bentonite, Cetearyl Alcohol, Aloe Barbadensis Leaf Juice (ORGANIC), Rubus Idaeus (Raspberry) Seed Oil (ORGANIC), Mauritia Flexuosa (Buriti) Fruit Oil (ORGANIC), Limnanthes Alba (Meadowfoam) Seed Oil, Rosmarinus Officinalis (Rosemary) Leaf Extract (ORGANIC), Helianthus Annuus (Sunflower) Seed Oil (ORGANIC), Bisabolol (ORGANIC), Brassica Campestris (Rapeseed) Seed Oil, Camelina Sativa Seed Oil, Opuntia Ficus-Indica Flower Extract, Carthamus Tinctorius (Safflower) Oleosomes, Shea Butter Ethyl Esters, Propanediol, Glycerin (ORGANIC), Coco-Glucoside, Laminaria Digitata (Algae) Extract (ORGANIC), Microcrystalline Cellulose, Cellulose Gum, Sodium Stearoyl Glutamate, Caprylhydroxamic Acid, Caprylyl Glycol, Capryloyl Glycerin/Sebacic Acid Copolymer, Citric Acid

QUESTIONS

Call 760-940-2125